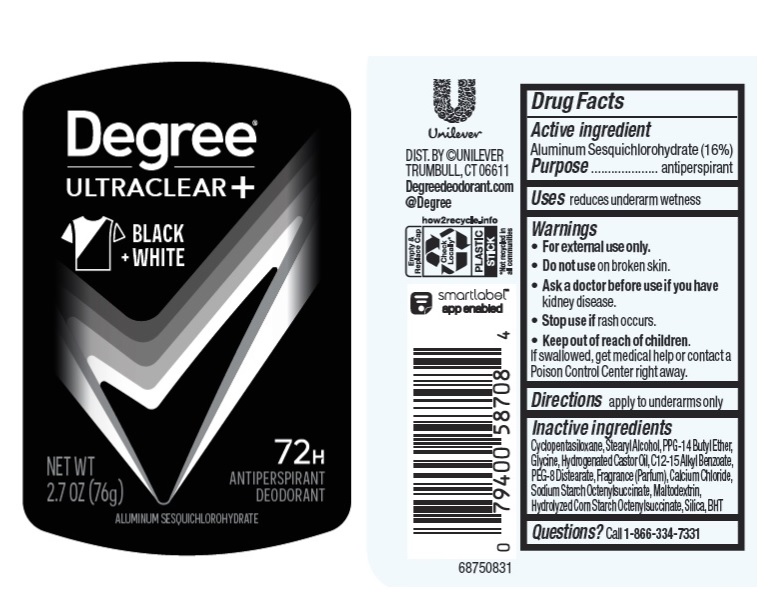 DRUG LABEL: Degree
NDC: 64942-1974 | Form: STICK
Manufacturer: Conopco Inc. d/b/a/ Unilever
Category: otc | Type: HUMAN OTC DRUG LABEL
Date: 20241108

ACTIVE INGREDIENTS: ALUMINUM SESQUICHLOROHYDRATE 16 g/100 g
INACTIVE INGREDIENTS: GLYCINE; HYDROGENATED CASTOR OIL; CALCIUM CHLORIDE; CYCLOMETHICONE 5; BUTYLATED HYDROXYTOLUENE; PEG-8 DISTEARATE; MALTODEXTRIN; PPG-14 BUTYL ETHER; STEARYL ALCOHOL; SILICON DIOXIDE; ALKYL (C12-15) BENZOATE

Degree Ultraclear+ Black+White 72H Antiperspirant Deodorant

Drug Facts

Active ingredient

Aluminum Sesquichlorohydrate (16%)

Purpose

antiperspirant

Uses

reduces underarm wetness

Warnings

• For external use only.
• Do not use on broken skin .
• Ask a doctor before use if you have kidney disease.
• Stop use if rash occurs.

• Keep out of reach of children.

If swallowed, get medical help or contact a Poison Control Center right away.

Directions

apply to underarms only

Inactive ingredients

Cyclopentasiloxane, Stearyl Alcohol, PPG-14 Butyl Ether, Glycine, Hydrogenated Castor Oil, C12-15 Alkyl Benzoate, PEG-8 Distearate, Fragrance (Parfum), Calcium Chloride, Sodium Starch Octenylsuccinate, Maltodextrin, Hydrolyzed Corn Starch Octenylsuccinate, Silica, BHT.

Questions?

Call 1-866-334-7331